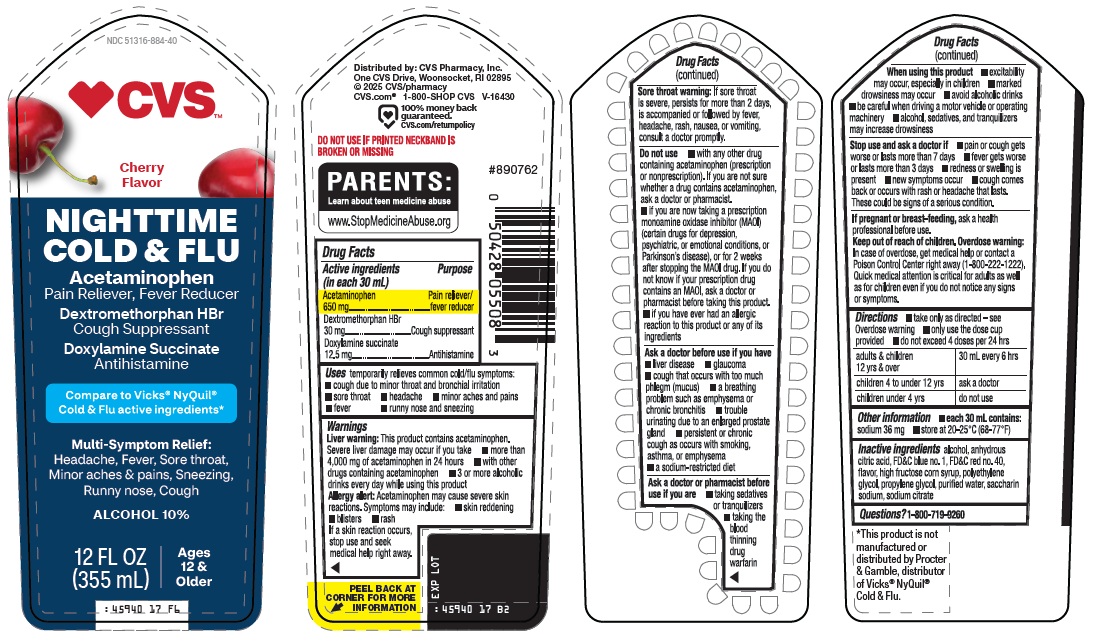 DRUG LABEL: NIGHTTIME COLD AND FLU
NDC: 51316-884 | Form: SOLUTION
Manufacturer: CVS WOONSOCKET PRESCRIPTION CENTER, INCORPORATED
Category: otc | Type: HUMAN OTC DRUG LABEL
Date: 20260217

ACTIVE INGREDIENTS: ACETAMINOPHEN 650 mg/30 mL; DEXTROMETHORPHAN HYDROBROMIDE 30 mg/30 mL; DOXYLAMINE SUCCINATE 12.5 mg/30 mL
INACTIVE INGREDIENTS: ALCOHOL; ANHYDROUS CITRIC ACID; FD&C BLUE NO. 1; FD&C RED NO. 40; HIGH FRUCTOSE CORN SYRUP; POLYETHYLENE GLYCOL, UNSPECIFIED; PROPYLENE GLYCOL; WATER; SACCHARIN SODIUM; SODIUM CITRATE, UNSPECIFIED FORM

CVS Pharmacy, Inc. Nighttime Cold & Flu Drug Facts

Active ingredients (in each 30 mL)

Acetaminophen 650 mg

Dextromethorphan HBr 30 mg

Doxylamine succinate 12.5 mg

Purpose

Pain reliever/fever reducer

Cough suppressant

Antihistamine

Uses

temporarily relieves common cold/flu symptoms:

- cough due to minor throat and bronchial irritation
- sore throat
- headache
- minor aches and pains
- fever
- runny nose and sneezing

Warnings

Liver warning: This product contains acetaminophen. Severe liver damage may occur if you take

- more than 4,000 mg of acetaminophen in 24 hours
- with other drugs containing acetaminophen
- 3 or more alcoholic drinks every day while using this product

Allergy alert: Acetaminophen may cause severe skin reactions. Symptoms may include:

- skin reddening
- blisters
- rash
  If a skin reaction occurs, stop use and seek medical help right away.

Sore throat warning: If sore throat is severe, persists for more than 2 days, is accompanied or followed by fever, headache, rash, nausea, or vomiting, consult a doctor promptly.

Do not use

- with any other drug containing acetaminophen (prescription or nonprescription). If you are not sure whether a drug contains acetaminophen, ask a doctor or pharmacist.
- if you are now taking a prescription monoamine oxidase inhibitor (MAOI) (certain drugs for depression, psychiatric, or emotional conditions, or Parkinson's disease), or for 2 weeks after stopping the MAOI drug. If you do not know if your prescription drug contains an MAOI, ask a doctor or pharmacist before taking this product.
- if you have ever had an allergic reaction to this product or any of its ingredients

Ask a doctor before use if you have

- liver disease
- glaucoma
- cough that occurs with too much phlegm (mucus)
- a breathing problem such as emphysema or chronic bronchitis
- trouble urinating due to an enlarged prostate gland
- persistent or chronic cough as occurs with smoking, asthma, or emphysema
- a sodium-restricted diet

Ask a doctor or pharmacist before use if you are

- taking sedatives or tranquilizers
- taking the blood thinning drug warfarin

When using this product

- excitability may occur, especially in children
- marked drowsiness may occur
- avoid alcoholic drinks
- be careful when driving a motor vehicle or operating machinery
- alcohol, sedatives, and tranquilizers may increase drowsiness

Stop use and ask a doctor if

- pain or cough gets worse or lasts more than 7 days
- fever gets worse or lasts more than 3 days
- redness or swelling is present
- new symptoms occur
- cough comes back or occurs with rash or headache that lasts. These could be signs of a serious condition.

If pregnant or breast-feeding,

ask a health professional before use.

Keep out of reach of children.

Overdose warning: In case of overdose, get medical help or contact a Poison Control Center right away (1-800-222-1222). Quick medical attention is critical for adults as well as for children even if you do not notice any signs or symptoms.

Directions

- take only as directed - see Overdose warning
- only use the dose cup provided
- do not exceed 4 doses per 24 hrs

adults & children 12 yrs & over | 30 mL every 6 hrs
children 4 to under 12 yrs | ask a doctor
children under 4 yrs | do not use

Other information

- each 30 mL contains: sodium 36 mg
- store at 20-25°C (68-77°F)

Inactive ingredients

alcohol, anhydrous citric acid, FD&C blue no. 1, FD&C red no. 40, flavor, high fructose corn syrup, polyethylene glycol, propylene glycol, purified water, saccharin sodium, sodium citrate

Questions?

1-800-719-9260

Package/Label Principal Display Panel

CVS™

Cherry Flavor

NIGHTTIME COLD & FLU

Acetaminophen

Pain Reliever, Fever Reducer

Dextromethorphan HBr

Cough Suppressant

Doxylamine Succinate

Antihistamine

Compare to Vicks® NyQuil® Cold & Flu active ingredients

Multi-Symptom Relief: Headache, Fever, Sore throat, Minor aches & pains, Sneezing, Runny nose, Cough

ALCOHOL 10%

12 FL OZ (355 mL)

Ages 12 & Older